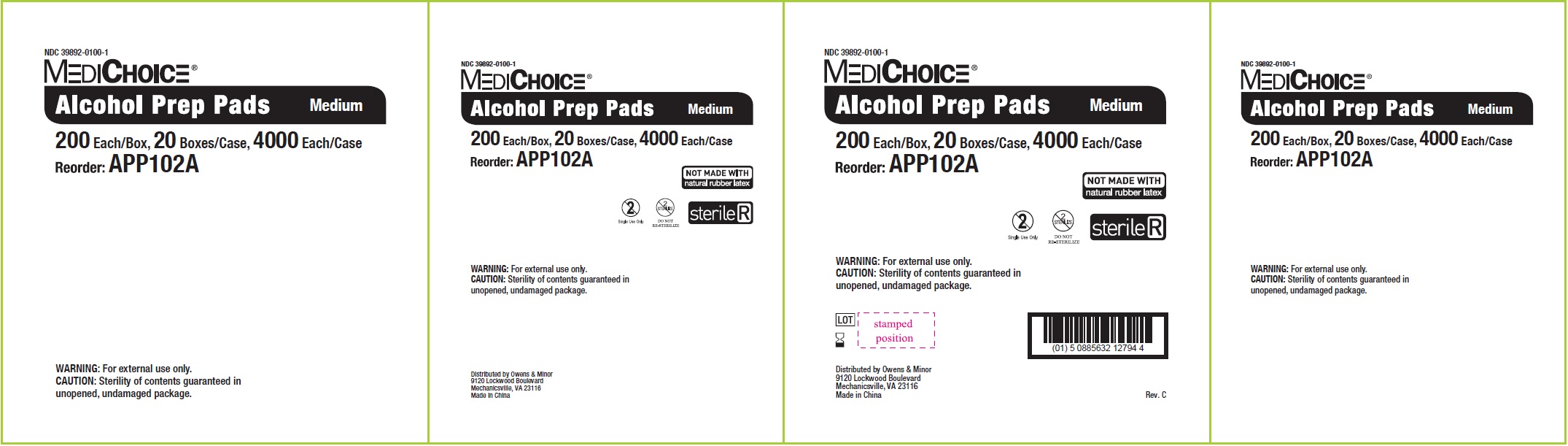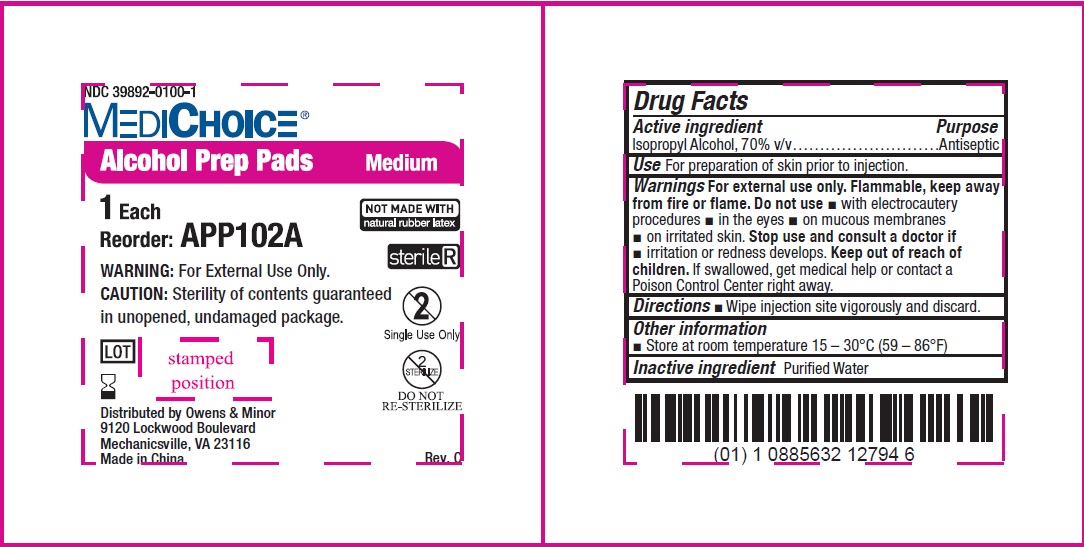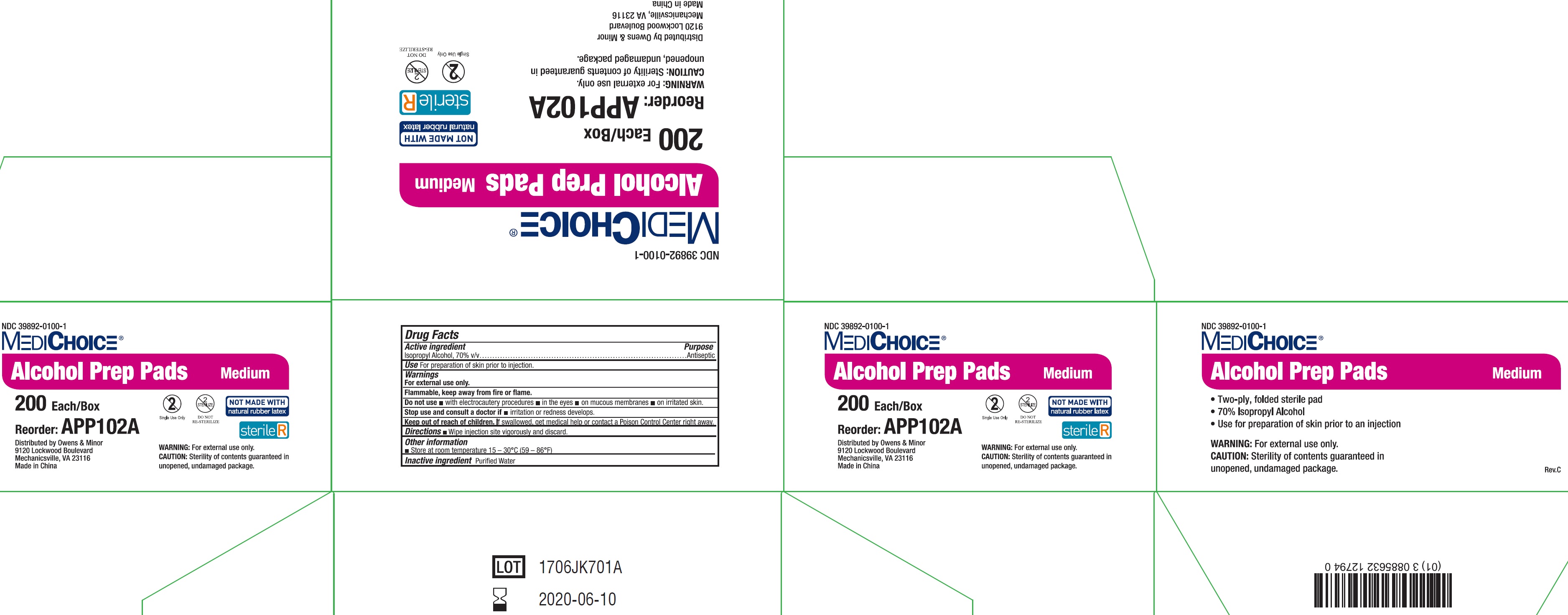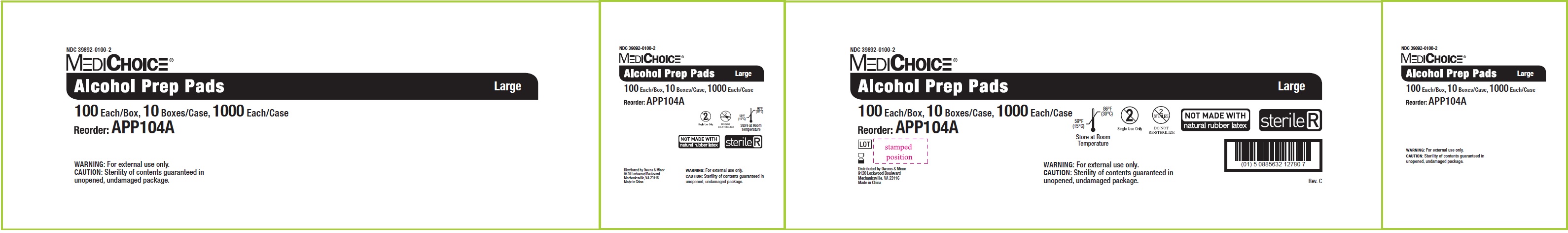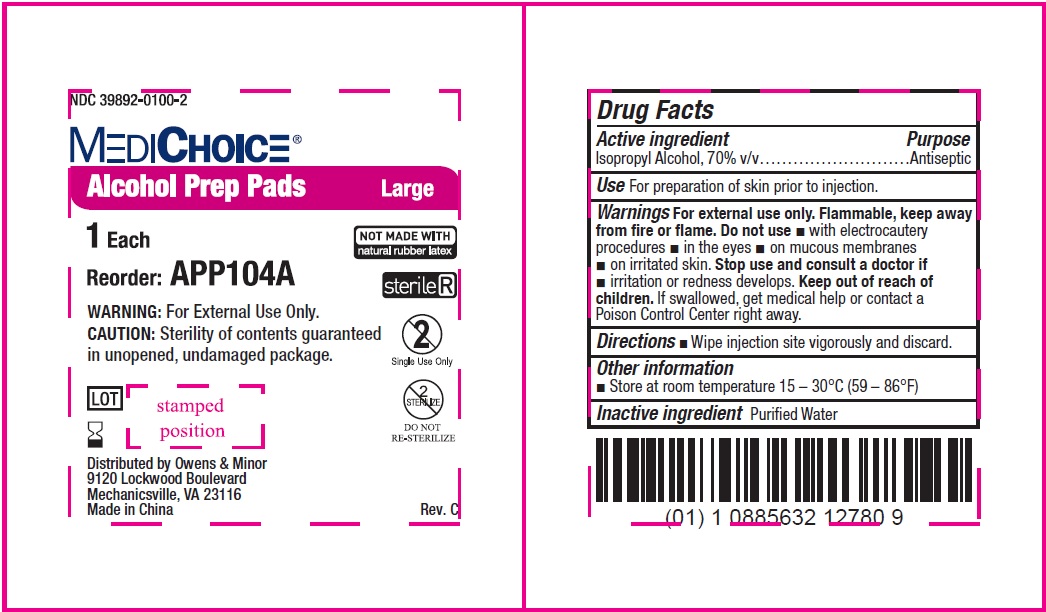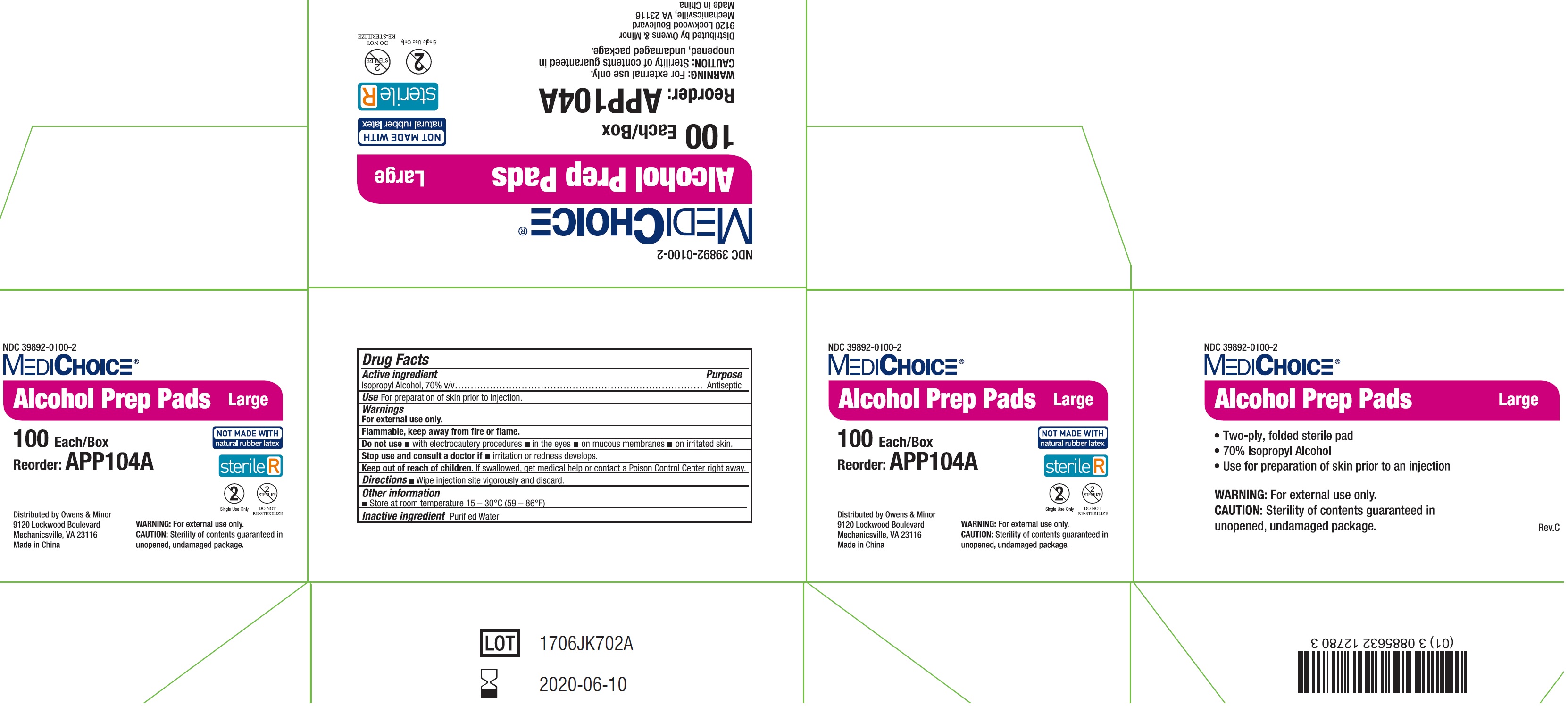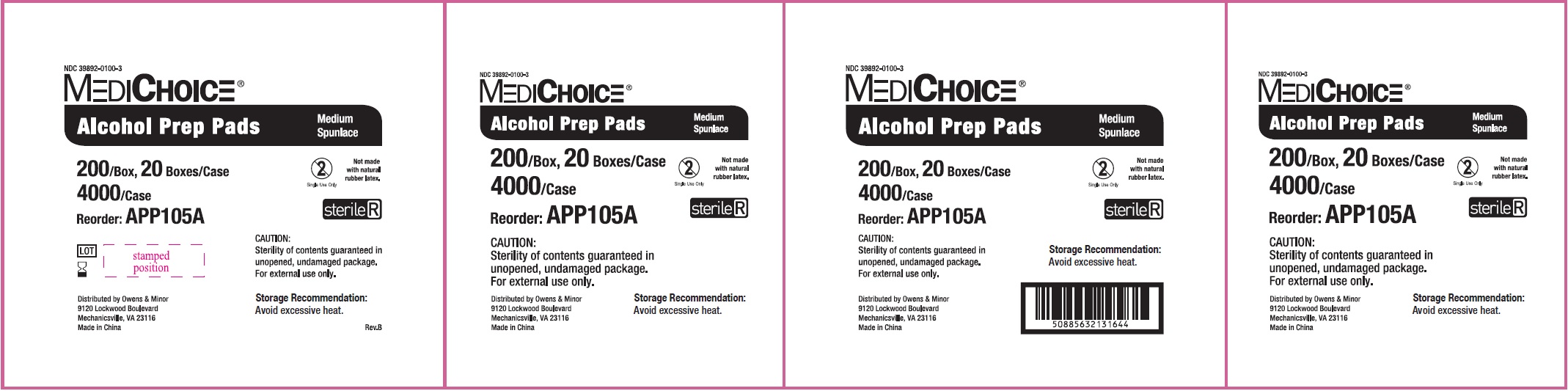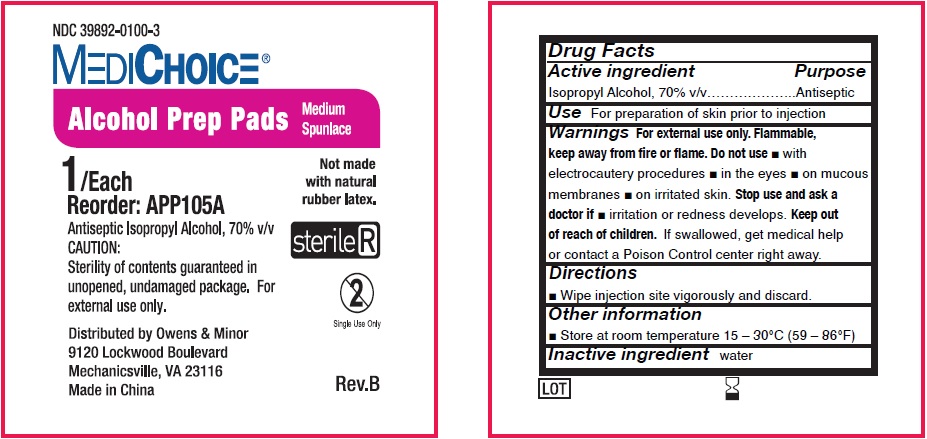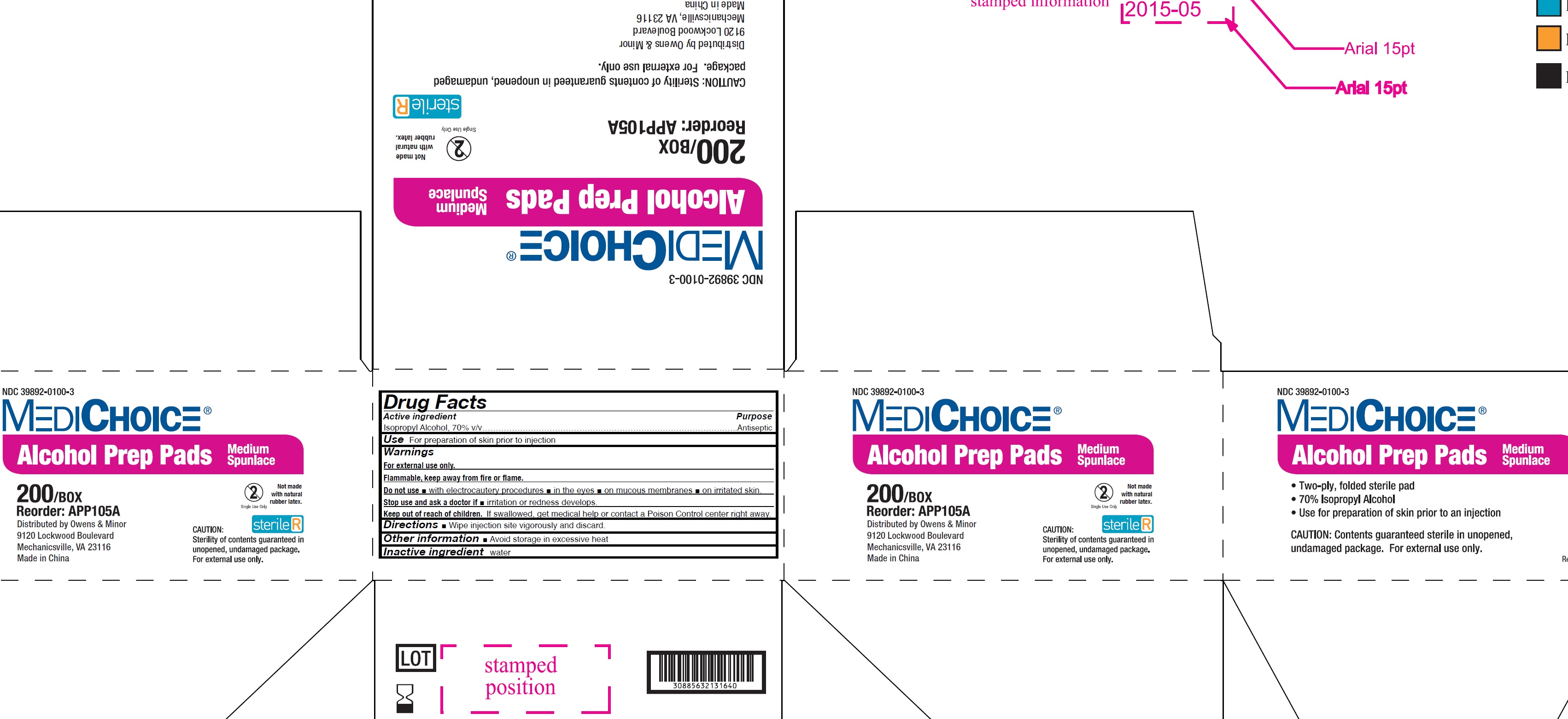 DRUG LABEL: MediChoice Antiseptic Isopropyl Alcohol Prep Pads
NDC: 39892-0100 | Form: SWAB
Manufacturer: O&M HALYARD, INC.
Category: otc | Type: HUMAN OTC DRUG LABEL
Date: 20251009

ACTIVE INGREDIENTS: ISOPROPYL ALCOHOL 70 mL/100 mL
INACTIVE INGREDIENTS: WATER

MediChoice Antiseptic Isopropyl Alcohol Prep Pads

Active Ingredient

Isopropyl Alcohol, 70% v/v

Purpose

Antiseptic

Use

For preparation of skin prior to injection.

Warnings

For external use only.

Flammable, keep away from fire or flame.

Do not use

- with electrocautery procedures
- in the eyes.
- on mucous membranes
- on irritated skin.

Stop use and ask a doctor if

- irritation and redness develops

Keep out of reach of children.

If swallowed, get medical help or contact a Poison Control Center right away.

Directions

- Wipe injection site vigorously and discard.

Other information

Store at room temperature 15-30ºC (59-86ºF)

Inactive Ingredient

Purified Water